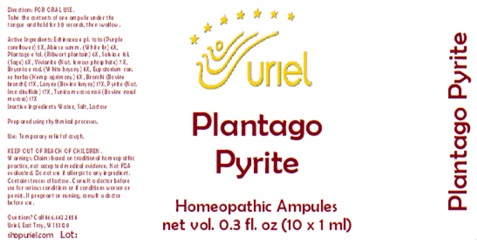 DRUG LABEL: Plantago Pyrite
NDC: 48951-8036 | Form: LIQUID
Manufacturer: Uriel Pharmacy Inc.
Category: homeopathic | Type: HUMAN OTC DRUG LABEL
Date: 20250916

ACTIVE INGREDIENTS: ECHINACEA, UNSPECIFIED 3 [hp_X]/1 mL; ABIES ALBA LEAFY TWIG 6 [hp_X]/1 mL; SAGE 6 [hp_X]/1 mL; FERROSOFERRIC PHOSPHATE 7 [hp_X]/1 mL; BRYONIA ALBA ROOT 8 [hp_X]/1 mL; EUPATORIUM PERFOLIATUM FLOWERING TOP 8 [hp_X]/1 mL; BEEF LUNG 17 [hp_X]/1 mL; PLANTAGO MAJOR LEAF 6 [hp_X]/1 mL; THYROID, BOVINE 17 [hp_X]/1 mL; FERROUS DISULFIDE 17 [hp_X]/1 mL; BOS TAURUS NASAL MUCOSA 17 [hp_X]/1 mL
INACTIVE INGREDIENTS: WATER; SODIUM CHLORIDE; LACTOSE

Plantago Pyrite

INDICATIONS AND USAGE

Directions: FOR ORAL USE.

DOSAGE AND ADMINISTRATION

Take the contents of one ampule under the tongue and hold for 30 seconds, then swallow.

ACTIVE INGREDIENT

Active Ingredients: Echinacea e pl. tota (Purple coneflower) 3X, Abies e summ. (White fir) 6X, Plantago e fol. (Ribwort plantain) 6X, Salvia e fol. (Sage) 6X, Vivianite (Nat. ferrous phosphate) 7X, Bryonia e rad. (White bryony) 8X, Eupatorium can. ex herba (Hemp agrimony) 8X, Bronchi (Bovine bronchi) 17X, Larynx (Bovine larynx) 17X, Pyrite (Nat. Iron disulfide) 17X, Tunica mucosa nasi (Bovine nasal mucosa) 17X

Inactive Ingredients: Water, Salt, Lactose

Prepared using rhythmical processes.

PURPOSE

Use: Temporary relief of cough.

KEEP OUT OF REACH OF CHILDREN.

WARNINGS

Warnings: Claims based on traditional homeopathic practice, not accepted medical evidence. Not FDA evaluated. Do not use if allergic to any ingredient. Contains traces of lactose. Consult a doctor before use for serious conditions or if conditions worsen or persist. If pregnant or nursing, consult a doctor before use.

Questions? Call 866.642.2858
Uriel, East Troy, WI 53120
shopuriel.com

Lot: